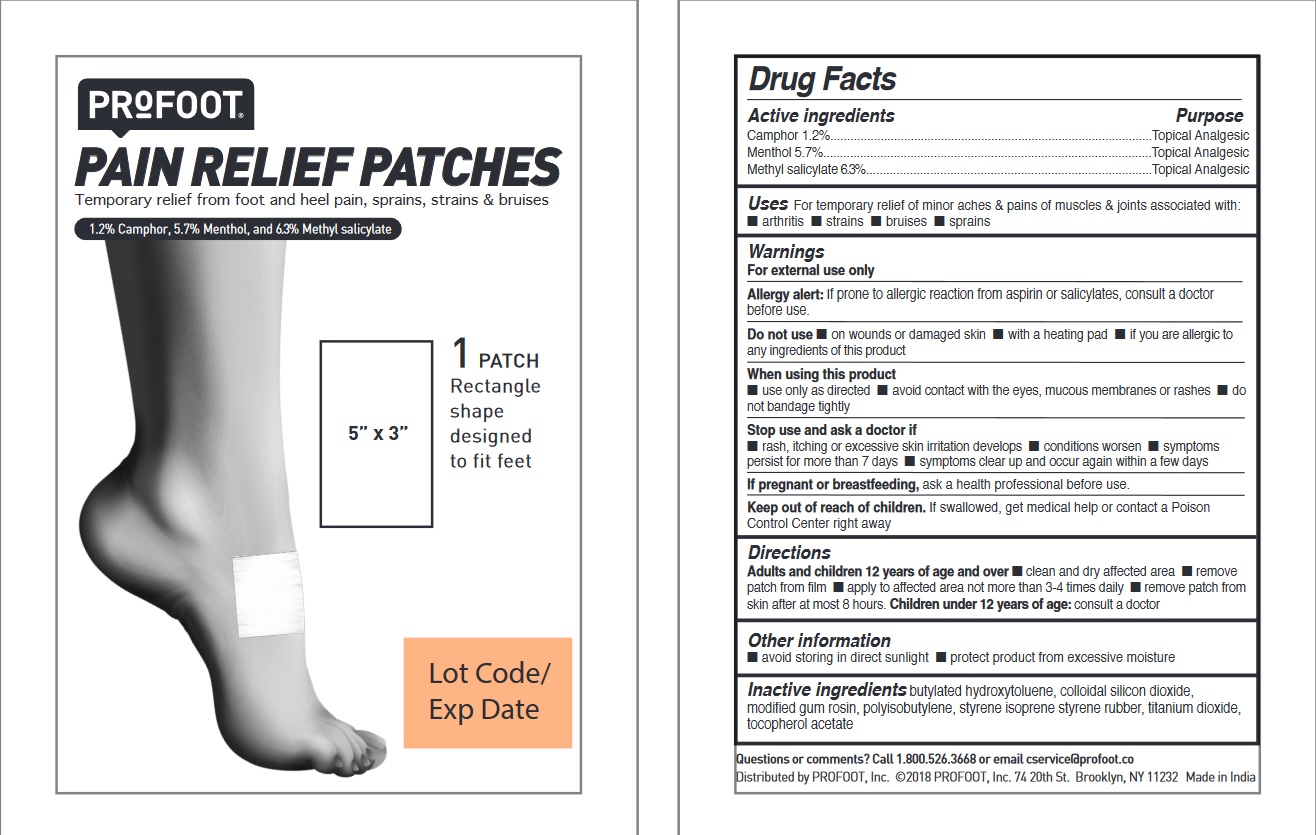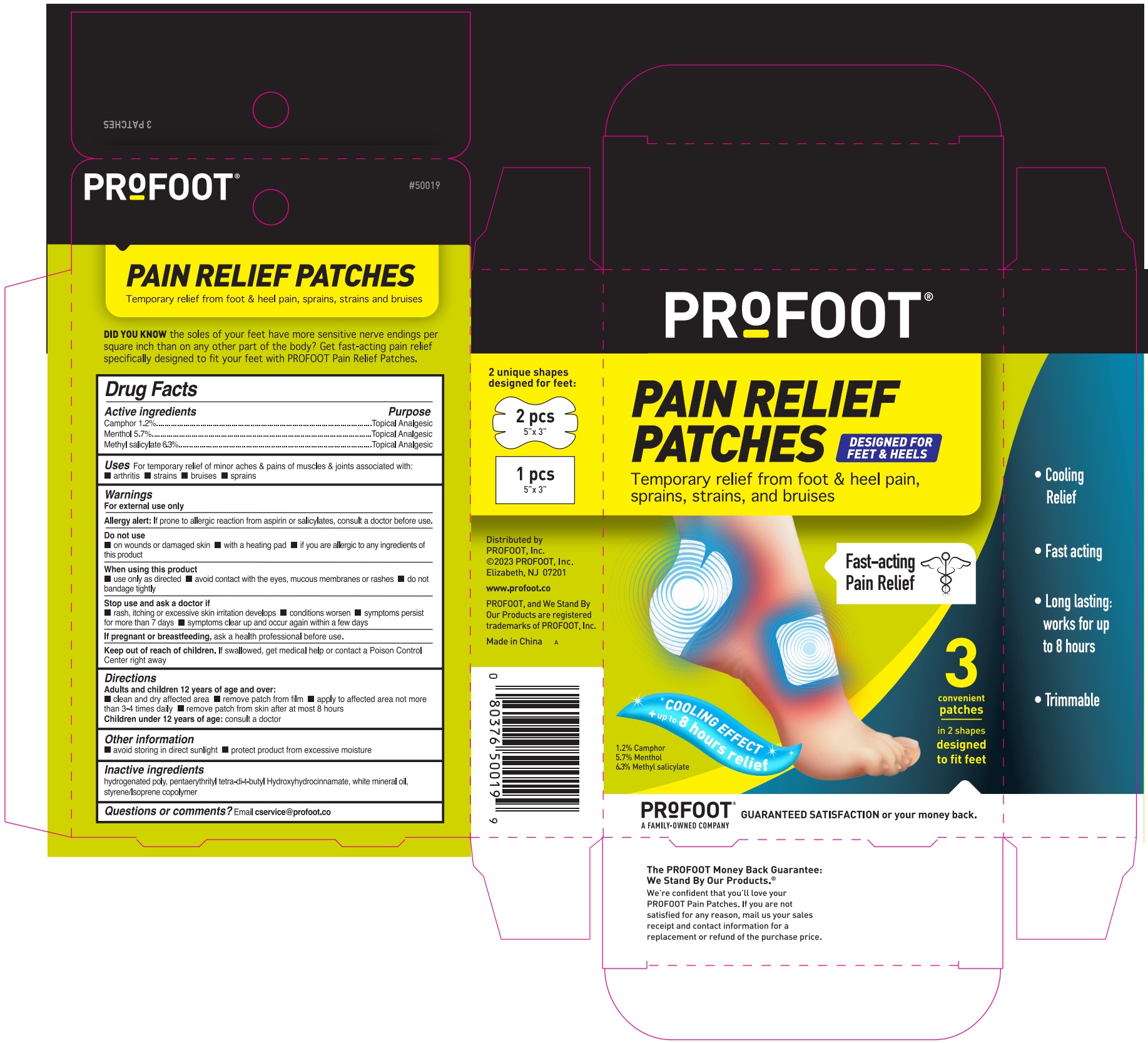 DRUG LABEL: Profoot Pain Relief Patches
NDC: 29784-601 | Form: KIT | Route: TOPICAL
Manufacturer: Profoot, Inc.
Category: otc | Type: HUMAN OTC DRUG LABEL
Date: 20241023

ACTIVE INGREDIENTS: METHYL SALICYLATE 63 mg/1 g; CAMPHOR (NATURAL) 12 mg/1 g; MENTHOL 57 mg/1 g; CAMPHOR (NATURAL) 12 mg/1 g; MENTHOL 57 mg/1 g; METHYL SALICYLATE 63 mg/1 g
INACTIVE INGREDIENTS: STYRENE/ISOPRENE/STYRENE BLOCK COPOLYMER; PENTAERYTHRITOL TETRAKIS(3-(3,5-DI-TERT-BUTYL-4-HYDROXYPHENYL)PROPIONATE); MINERAL OIL; HYDROGENATED C6-20 POLYOLEFIN (100 CST); MINERAL OIL; PENTAERYTHRITOL TETRAKIS(3-(3,5-DI-TERT-BUTYL-4-HYDROXYPHENYL)PROPIONATE); HYDROGENATED C6-20 POLYOLEFIN (100 CST); STYRENE/ISOPRENE/STYRENE BLOCK COPOLYMER

Profoot Pain Relief Patches

Active ingredients

Camphor 1.2%

Menthol 5.7%

Methyl salicylate 6.3%

Purpose

Topical Analgesic

Topical Analgesic

Topical Analgesic

INDICATIONS AND USAGE

Uses For temporary relief of minor aches & pains of muscles & joints associated with:

•arthritis •strains •bruises •sprains

Warnings

For external use only

Allergy alert: If prone to allergic reaction from aspirin or salicylates, consult a doctor before use.

Do not use

• on wounds or damaged skin • with a heating pad • if you are allergic to any of the ingredients of

this product

When using this product

• use only as directed • avoid contact with the eyes, mucous membranes or rashes • do not

bandage tightly

Stop use and ask a doctor if

• rash, itching or excessive skin irritation develops • condition worsens •symptoms persist

for more than 7 days • symptoms clear up and occur again within a few days

If pregnant or breastfeeding, ask a health professional before use.

Keep out of reach of children. If swallowed, get medical help or contact a Poison Control

Center right away

Directions

Adults and children 12 years of age and over:

• clean and dry affected area • remove patch from film • apply to affected area not more

than 3-4 times daily • remove patch from skin after at most 8 hours

Children under 12 years of age: consult a doctor

Other information

• avoid storing in direct sunlight • protect product from excessive moisture

INACTIVE INGREDIENT

Inactive ingredients hydrogenated poly, pentaerythrityl tetra-di-t-butyl Hydroxyhydrocinnamate, white mineral oil, styrene/Isoprene copolymer

Questions or comments? Email cservice@profoot.co